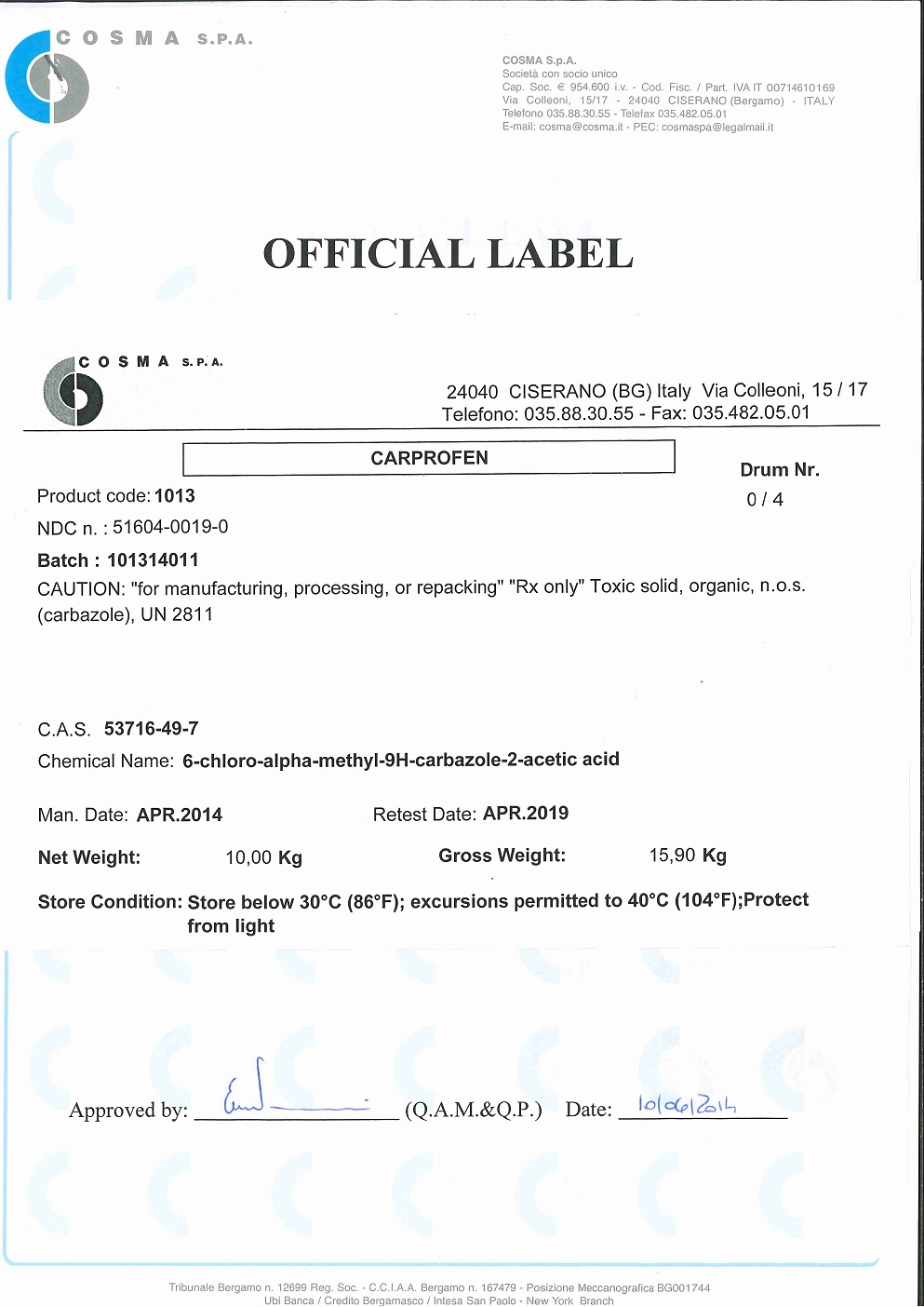 DRUG LABEL: Carprofen
NDC: 51604-0019 | Form: POWDER
Manufacturer: COSMA Spa
Category: other | Type: BULK INGREDIENT - ANIMAL DRUG
Date: 20231106

ACTIVE INGREDIENTS: CARPROFEN 30 kg/30 kg

Carprofen

PACKAGE LABEL

COSMA S.P.A. 24040 CISERANO (BG) Italy Via Colleoni, 15/17

Telefono: 035.88.30.55 - Fax: 035.482.05.01

Product code: 1013 Drum Nr. 0/4

NDC n: 51604-0019-0

Batch:

CAUTION: "for manufacturing, processing, or repacking" "Rx only" Toxic solid, organic, no.o.s (carbazole, UN 2811

CAS 53716-49-7

Chemical name: 6-chloro-alpha-methyl-9H-carbazole-2-acetic acid

Man Date: Retest Date:

Net Weight: Gross Weight:

Store Conditions: Store below 30°C (86°F); excursions permitted to 40°C (104°F); Protect from light